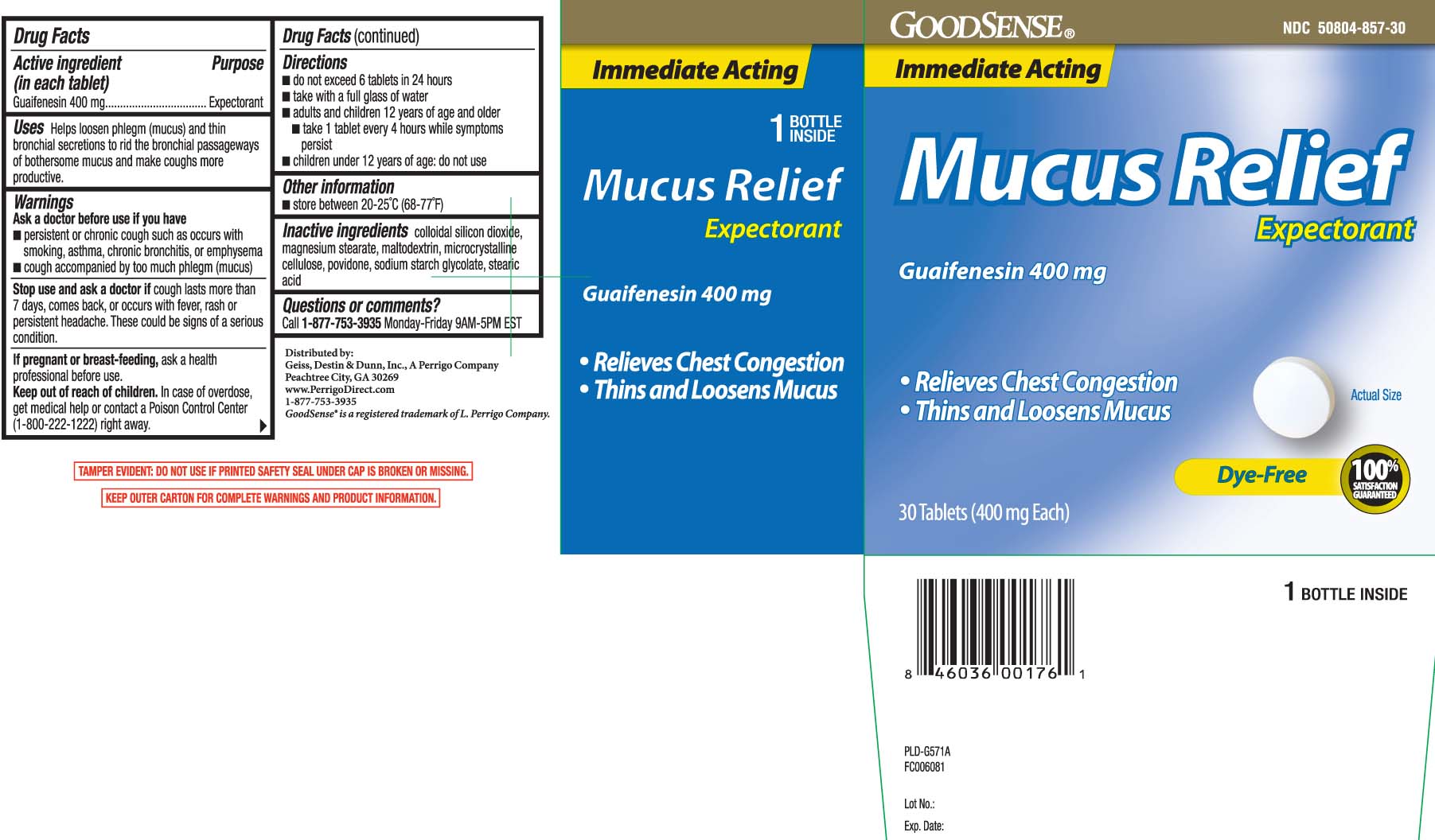 DRUG LABEL: Mucus Relief
NDC: 50804-857 | Form: TABLET
Manufacturer: Good Sense (Geiss, Destin & Dunn, Inc.)
Category: otc | Type: HUMAN OTC DRUG LABEL
Date: 20250811

ACTIVE INGREDIENTS: GUAIFENESIN 400 mg/1 1
INACTIVE INGREDIENTS: SILICON DIOXIDE; MAGNESIUM STEARATE; MALTODEXTRIN; CELLULOSE, MICROCRYSTALLINE; POVIDONE; SODIUM STARCH GLYCOLATE TYPE A CORN; STEARIC ACID

Drug Facts

Active ingredient (in each tablet)

Guaifenesin 400 mg

Purpose

Expectorant

Uses

Helps loosen phlegm (mucus) and thin bronchial secretions to rid the bronchial passageways of bothersome mucus and makes coughs more productive.

Warnings

Ask a doctor before use if you have

- persistent or chronic cough such as occurs with smoking, asthma, chronic bronchitis or emphysema
- cough accopanied by too much phlegm (mucus)

Stop use and ask a doctor if

cough lasts more than 7 days, comes back, or occurs with fever, rash or persistent headache.

These could be signs of a serious condition.

If pregnant or breast-feeding,

ask a health professional before use.

Keep out of reach of children.

In case of overdose, get medical help or contact a Poison Control Center (1-800-222-1222) right away.

Directions

- do not exceed 6 tablets in 24 hours
- take with a full glass of water
- adults and children 12 years of age and older
  - take 1 tablet every 4 hours while symptoms persist
- children under 12 years of age: do not use

Other information

- store between 20-25ºC (68-77ºF)

Inactive ingredients

colloidal silicon dioxide, magnesium stearate, maltodextrin, microcrystalline cellulose, povidone, sodium starch glycolate, stearic acid

Questions or comments?

Call 1-877-753-3935 Monday-Friday 9AM-5PM EST

Principal Display Panel

Immediate Acting

Mucus Relief

Expectorant

Guaifenesin 400 mg TABLETS

- Relieves Chest Congestion
- Thin & Loosens Mucus

Dye-Free

TABLETS

TAMPER EVIDENT: DO NOT USE IF PRINTED SAFETY SEAL UNDER CAP IS BROKEN OR MISSING.

KEEP OUTER CARTON FOR COMPLETE WARNINGS AND PRODUCT INFORMATION.

Distributed by:

Geiss, Destin & Dunn. Inc., A Perrigo Company

Peachtree City, GA 30269

www.PerrigoDirect.com

Package Label

GOOD SENSE Mucus Relief Tablets